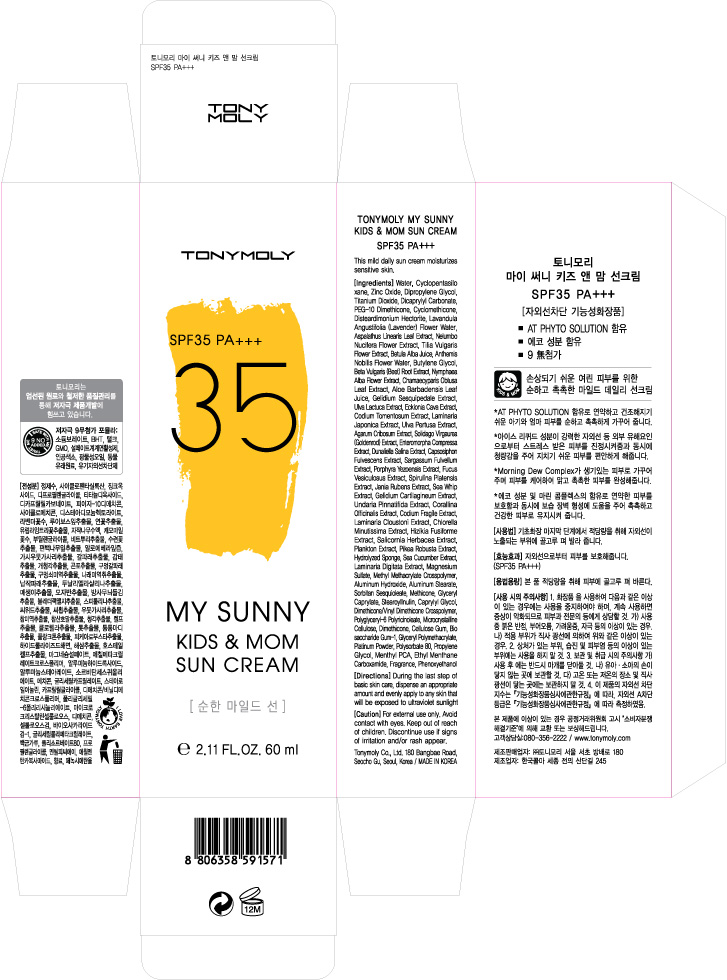 DRUG LABEL: TONYMOLY My Sunny Kids and Mom Sun Cream
NDC: 59078-124 | Form: CREAM
Manufacturer: Tonymoly Co., Ltd.
Category: otc | Type: HUMAN OTC DRUG LABEL
Date: 20160204

ACTIVE INGREDIENTS: ZINC OXIDE 27466.56 mg/60 mL; TITANIUM DIOXIDE 14745.78 mg/60 mL
INACTIVE INGREDIENTS: LAMINARIA DIGITATA; CHAMAEMELUM NOBILE FLOWER; ASPALATHUS LINEARIS LEAF; LAVENDER OIL; AGARUM CLATHRATUM; SOLIDAGO VIRGAUREA FLOWERING TOP; DICAPRYLYL CARBONATE; CYCLOMETHICONE; MAGNESIUM SULFATE; ALUMINUM HYDROXIDE; ALUMINUM STEARATE; SORBITAN SESQUIOLEATE; PHENOXYETHANOL; CAPRYLYL GLYCOL; GLYCERYL CAPRYLATE; WATER; BIOSACCHARIDE GUM-1; NYMPHAEA ALBA FLOWER; NELUMBO NUCIFERA FLOWER; BUTYLENE GLYCOL; PROPYLENE GLYCOL; ETHYL MENTHANE CARBOXAMIDE; PIKEA ROBUSTA; CAPSOSIPHON FULVESCENS; CHLORELLA MINUTISSIMA; CODIUM FRAGILE; CODIUM TOMENTOSUM; DUNALIELLA SALINA; FUCUS VESICULOSUS; GELIDIUM CARTILAGINEUM; SPIRULINA PLATENSIS; ULVA LACTUCA; DISTEARDIMONIUM HECTORITE; DIMETHICONE; GELIDIUM SESQUIPEDALE; UNDARIA PINNATIFIDA; CORALLINA OFFICINALIS; CHAMAECYPARIS OBTUSA LEAF; ECKLONIA CAVA; PORPHYRA YEZOENSIS; SARGASSUM FULVELLUM; SEA CUCUMBER, UNSPECIFIED; SOLIDAGO VIRGAUREA WHOLE; POLYSORBATE 80; LAVANDULA ANGUSTIFOLIA FLOWER; CARBOXYMETHYLCELLULOSE SODIUM; BETULA PUBESCENS RESIN; BEET; SALICORNIA EUROPAEA; TILIA X EUROPAEA FLOWER; ALOE VERA LEAF; MENTHYL PYRROLIDONE CARBOXYLATE, (-),DL-; ULVA COMPRESSA; SARGASSUM FUSIFORME; LAMINARIA HYPERBOREA; LAMINARIA JAPONICA; PLATINUM

Active Ingredients

Dipropylene Glycol 7.00%, Titanium Dioxide 5.81%, Zinc Oxide 8.16%

Purpose

Sunscreen

Use

This mild daily sun cream moisturizes sensitive skin.

Caution

For external use only. Avoid contact with eyes. Keep out of reach of children. Discontinue use if signs of irritation and/or rash appear.

Keep out of reach of children

Directions

During the last step of basic skin care, dispense an appropriate amount and evenly apply to any skin that will be exposed to ultraviolet sunlight.

Inactive Ingredients

WATER, CYCLOPENTASILOXANE, DICAPRYLYL CARBONATE, PEG-10 DIMETHICONE, CYCLOMETHICONE, DISTEARDIMONIUM HECTORITE, MAGNESIUM SULFATE, METHYL METHACRYLATE CROSSPOLYMER, ALUMINUM HYDROXIDE, ALUMINUM STEARATE, SORBITAN SESQUIOLEATE, PHENOXYETHANOL, METHICONE, CAPRYLYL GLYCOL, GLYCERYL CAPRYLATE, STEAROYL INULIN, DIMETHICONE/VINYL DIMETHICONE CROSSPOLYMER, FRAGRANCE, POLYGLYCERYL-6 POLYRICINOLEATE, MICROCRYSTALLINE CELLULOSE, DIMETHICONE, CELLULOSE GUM, BIOSACCHARIDE GUM-1, ANTHEMIS NOBILIS FLOWER WATER, ASPALATHUS LINEARIS LEAF EXTRACT, BETULA ALBA JUICE, LAVANDULA ANGUSTIFOLIA (LAVENDER) FLOWER WATER, NELUMBO NUCIFERA FLOWER EXTRACT, TILIA VULGARIS FLOWER EXTRACT, BUTYLENE GLYCOL, BETA VULGARIS (BEET) ROOT EXTRACT, CHAMAECYPARIS OBTUSA LEAF EXTRACT, NYMPHAEA ALBA FLOWER EXTRACT, ALOE BARBADENSIS LEAF JUICE, GLYCERYL POLYMETHACRYLATE, PROPYLENE GLYCOL, MENTHYL PCA, ETHYL MENTHANE CARBOXAMIDE, AGARUM CRIBOSUM EXTRACT, CAPSOSIPHON FULVESCENS EXTRACT, CHLORELLA MINUTISSIMA EXTRACT, CODIUM FRAGILE EXTRACT, CODIUM TOMENTOSUM EXTRACT, CORALLINA OFFICINALIS EXTRACT, DUNALIELLA SALINA EXTRACT, ECKLONIA CAVA EXTRACT, ENTEROMORPHA COMPRESSA EXTRACT, FUCUS VESICULOSUS EXTRACT, GELIDIUM CARTILAGINEUM EXTRACT, GELIDIUM SESQUIPEDALE EXTRACT, HIZIKIA FUSIFORME EXTRACT, HYDROLYZED SPONGE, JANIA RUBENS EXTRACT, LAMINARIA CLOUSTONI EXTRACT, LAMINARIA DIGITATA EXTRACT, LAMINARIA JAPONICA EXTRACT, PIKEA ROBUSTA EXTRACT, PLANKTON EXTRACT, PORPHYRA YEZOENSIS EXTRACT, SALICORNIA HERBACEA EXTRACT, SARGASSUM FULVELLUM EXTRACT, SEA CUCUMBER EXTRACT, SEA WHIP EXTRACT, SOLIDAGO VIRGAUREA (GOLDENROD) EXTRACT, SPIRULINA PLATENSIS EXTRACT, ULVA LACTUCA EXTRACT, ULVA PERTUSA EXTRACT, UNDARIA PINNATIFIDA EXTRACT, PLATINUM POWDER, POLYSORBATE 80